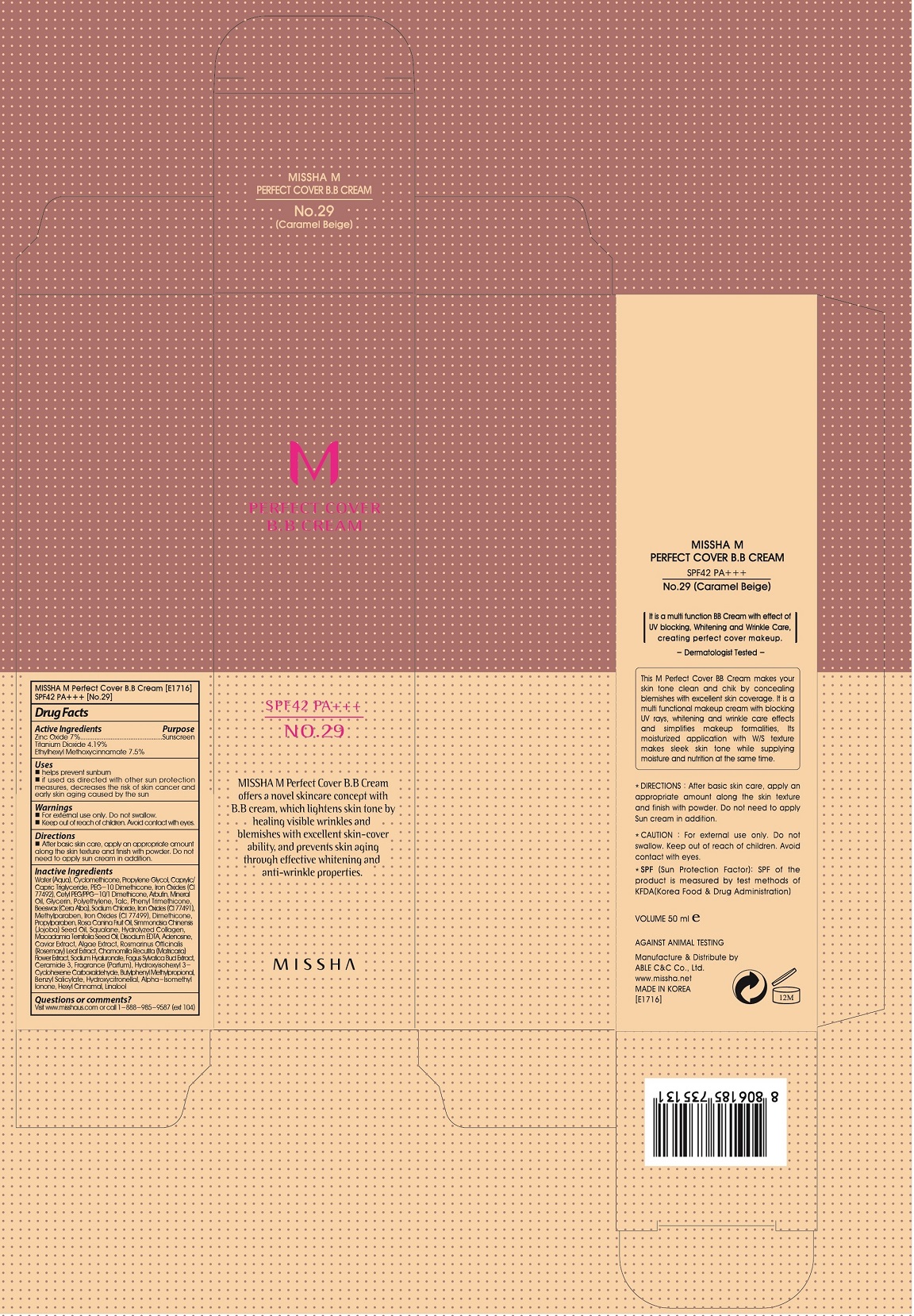 DRUG LABEL: MISSHA M Perfect Cover BB SPF42 No29
NDC: 13733-245 | Form: CREAM
Manufacturer: Able C&C Co., Ltd.
Category: otc | Type: HUMAN OTC DRUG LABEL
Date: 20241205

ACTIVE INGREDIENTS: OCTINOXATE 0.075 g/1 g; TITANIUM DIOXIDE 0.042 g/1 g; ZINC OXIDE 0.07 g/1 g
INACTIVE INGREDIENTS: FERROSOFERRIC OXIDE; PEG-10 DIMETHICONE (600 CST); CYCLOMETHICONE; HIGH DENSITY POLYETHYLENE; GLYCERIN; FERRIC OXIDE RED; ARBUTIN; WATER; MINERAL OIL; TRIS(TRIMETHYLSILOXY)PHENYLSILANE; METHYLPARABEN; CETYL PEG/PPG-10/1 DIMETHICONE (HLB 2); PROPYLENE GLYCOL; SODIUM CHLORIDE; MEDIUM-CHAIN TRIGLYCERIDES; DIMETHICONE; FERRIC OXIDE YELLOW; YELLOW WAX; CERAMIDE 6 II; TALC

MISSHA M Perfect Cover BB Cream SPF42 No 29

ACTIVE INGREDIENTS

Octinoxate 7.5%

Zinc Oxide 7%

Titanium Dioxide 4.19%

PURPOSE

Sunscreen

Uses

- helps prevent sunburn
- if used as directed with other sun protection measures(see Directions), decreases the risk of skin cancer and early skin aging caused by the sun

Directions

- apply liberally 15 minutes before sun exposure
- reapply at least every 2 hours
- use a water-resistant sunscreen if swimming or sweating

Sun Protection Measures. Spending time in the sun increases your risk of skin cancer and early skin againg. To decrease this risk, regularly use a sunscreen with SPF value of 15 or higher and other sun protection measures including:

- limit time in the sun, especially from 10a.m.-2p.m.
- wear long-sleeved shirts, pants, hats and sunglasses

Other Information

protect the product in this container from excessive heat and direct sun

Inactive Ingredient

Water (Aqua), Cyclomethicone, Propylene Glycol, Caprylic/Capric Triglyceride, PEG-10 Dimethicone, Iron Oxides (CI 77492), Cetyl PEG/PPG-10/1 Dimethicone, Arbutin, Mineral Oil, Glycerin, Polyethylene, Talc, Phenyl Trimethicone, Beeswax (Cera Alba), Sodium Chloride, Sodium Chloride, Sodium Chloride, Sodium Chloride, Sodium Chloride

Questions of comments?

Visit www.misshaus.com or call 1-888-985-9887(Ext 104)

Warnings:
Do not use on damaged or broken skin.
When using this product, keep out of eyes. Rinse with water to Remove.
Stop use and ask a doctor, if rash ocurs.

Keep out of reach of children.